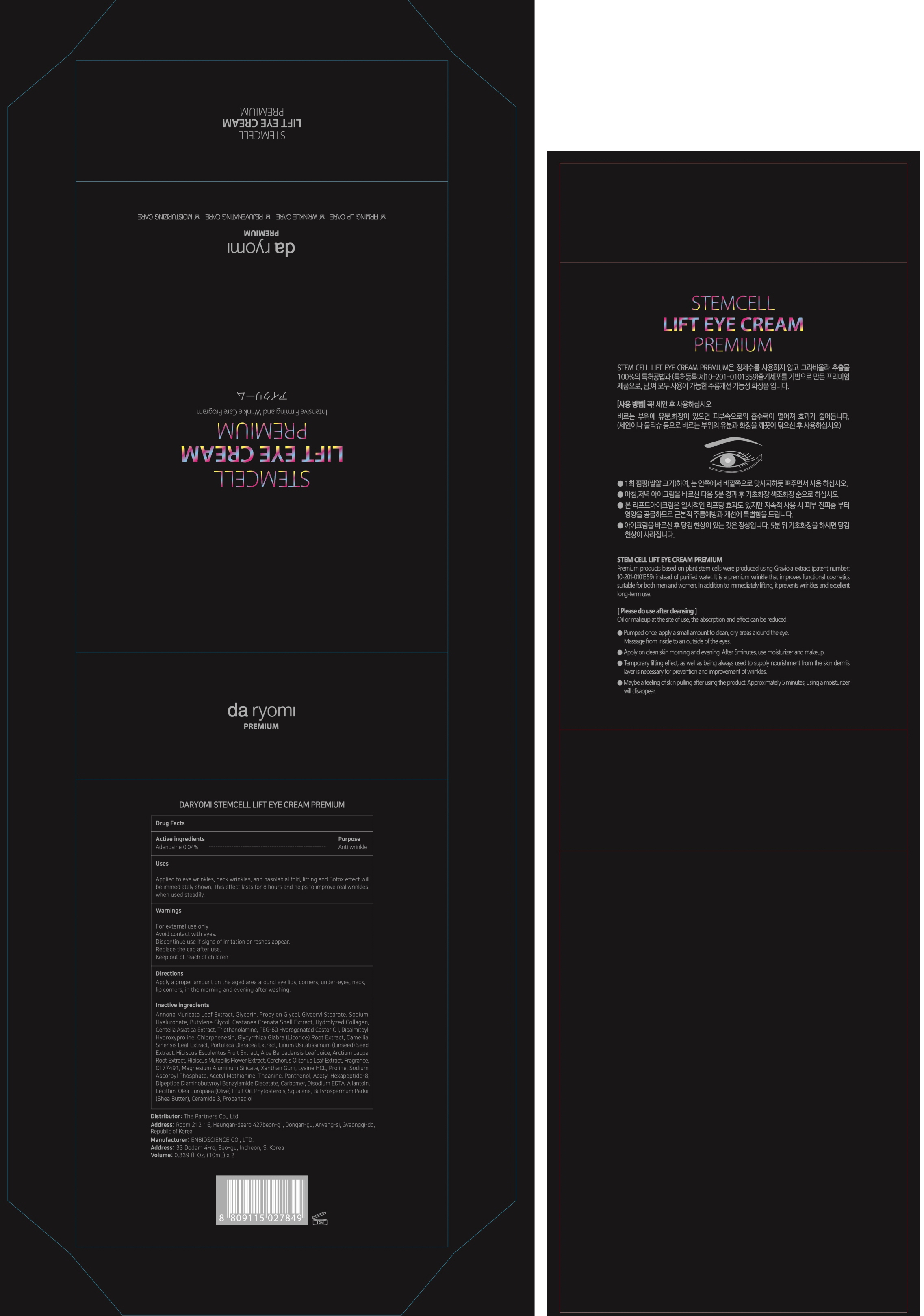 DRUG LABEL: DARYOMI STEMCELL LIFT EYE PREMIUM
NDC: 90034-010 | Form: CREAM
Manufacturer: The Partners Co., Ltd.
Category: otc | Type: HUMAN OTC DRUG LABEL
Date: 20201015

ACTIVE INGREDIENTS: Adenosine 0.004 g/10 mL
INACTIVE INGREDIENTS: Glycerin; PROPYLENE GLYCOL

ACTIVE INGREDIENT

Adenosine 0.04%

INACTIVE INGREDIENTS

Annona Muricata Leaf Extract, Glycerin, Propylen Glycol, Glyceryl Stearate, Sodium Hyaluronate, Butylene Glycol, Castanea Crenata Shell Extract, Hydrolyzed Collagen, Centella Asiatica Extract, Triethanolamine, PEG-60 Hydrogenated Castor Oil, Dipalmitoyl Hydroxyproline, Chlorphenesin, Glycyrrhiza Glabra (Licorice) Root Extract, Camellia Sinensis Leaf Extract, Portulaca Oleracea Extract, Linum Usitatissimum (Linseed) Seed Extract, Hibiscus Esculentus Fruit Extract, Aloe Barbadensis Leaf Juice, Arctium Lappa Root Extract, Hibiscus Mutabilis Flower Extract, Corchorus Olitorius Leaf Extract, Fragrance, CI 77491, Magnesium Aluminum Silicate, Xanthan Gum, Lysine HCL, Proline, Sodium Ascorbyl Phosphate, Acetyl Methionine, Theanine, Panthenol, Acetyl Hexapeptide-8, Dipeptide Diaminobutyroyl Benzylamide Diacetate, Carbomer, Disodium EDTA, Allantoin, Lecithin, Olea Europaea (Olive) Fruit Oil, Phytosterols, Squalane, Butyrospermum Parkii (Shea Butter), Ceramide 3, Propanediol

PURPOSE

Anti wrinkle

WARNINGS

For external use only
Avoid contact with eyes.
Discontinue use if signs of irritation or rashes appear.
Replace the cap after use.
Keep out of reach of children

KEEP OUT OF REACH OF CHILDREN

Uses

■ Applied to eye wrinkles, neck wrinkles, and nasolabial fold, lifting and Botox effect will be immediately shown. This effect lasts for 8 hours and helps to improve real wrinkles when used steadily.

Directions

Apply a proper amount on the aged area around eye lids, corners, under-eyes, neck, lip corners, in the morning and evening after washing.